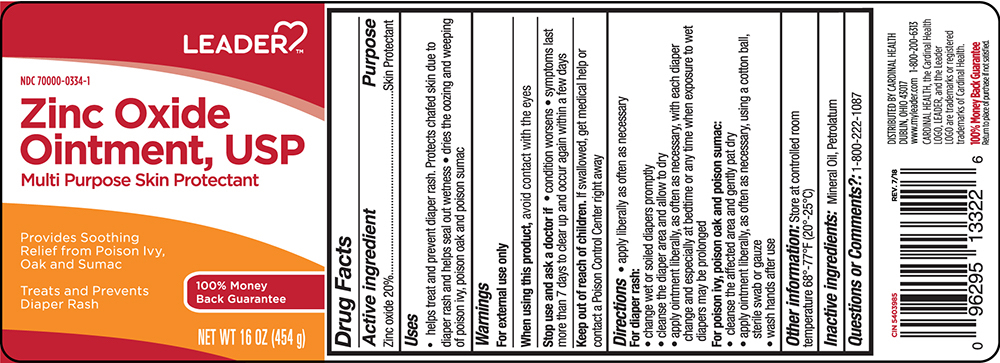 DRUG LABEL: Leader Zinc Oxide
NDC: 70000-0334 | Form: OINTMENT
Manufacturer: Cardinal Health 110,Inc.
Category: otc | Type: HUMAN OTC DRUG LABEL
Date: 20240118

ACTIVE INGREDIENTS: ZINC OXIDE 200 mg/1 g
INACTIVE INGREDIENTS: MINERAL OIL; PETROLATUM

Drug Facts

Active Ingredient

Zinc oxide 20%

Purpose

Skin Protectant

Uses

- helps treat and prevent diaper rash. Protects chafed skin due to diaper rash and helps seal out wetness.
- dries the oozing and weeping of poison ivy, poison oak and poison sumac.

Warnings

For external use only

When using this product, avoid contact with the eyes

Stop use and ask a doctor if

- condition worsens
- symptoms last more than 7 days to clear up and occur again within a few days

Keep out of reach of children. If swallowed, get medical help or contact a poison control center right away.

Directions

- apply liberally as often as necessary

For Diaper Rash

- change wet or soiled diapers promptly
- cleanse the diaper area and allow to dry
- apply ointment liberally, as often as necessary, with each diaper change and especially at bedtime or anytime when exposure to wet diapers may be prolonged

For Poison Ivy, poison oak and poison sumac;

- cleanse the affect area and pat dry
- apply ointment liberally, as often as necessary, using a cotton ball, sterile swab or gauze
- wash hands after use.

Inactive ingredients

mineral oil, petrolatum

Questions or comments?

Call 1-800-222-1087

Store at room temperature 20 - 25°C (68° - 77°F).

Principal Display Panel – Jar Label

Leader® NDC 70000-0334-1

Zinc Oxide

Ointment USP•

Multi Purpose Skin Protectant

provides soothing relief from poison ivy,

oak and sumac

Treats and prevents diaper rash

Net Wt 1 lb (454 g)